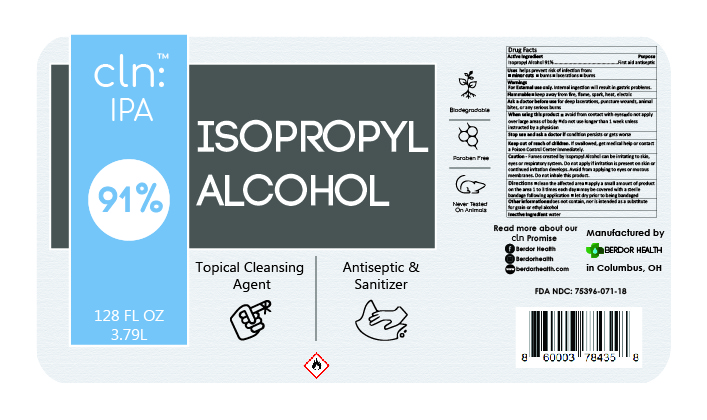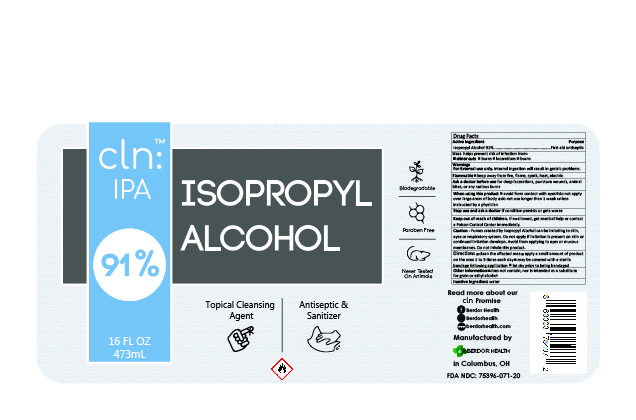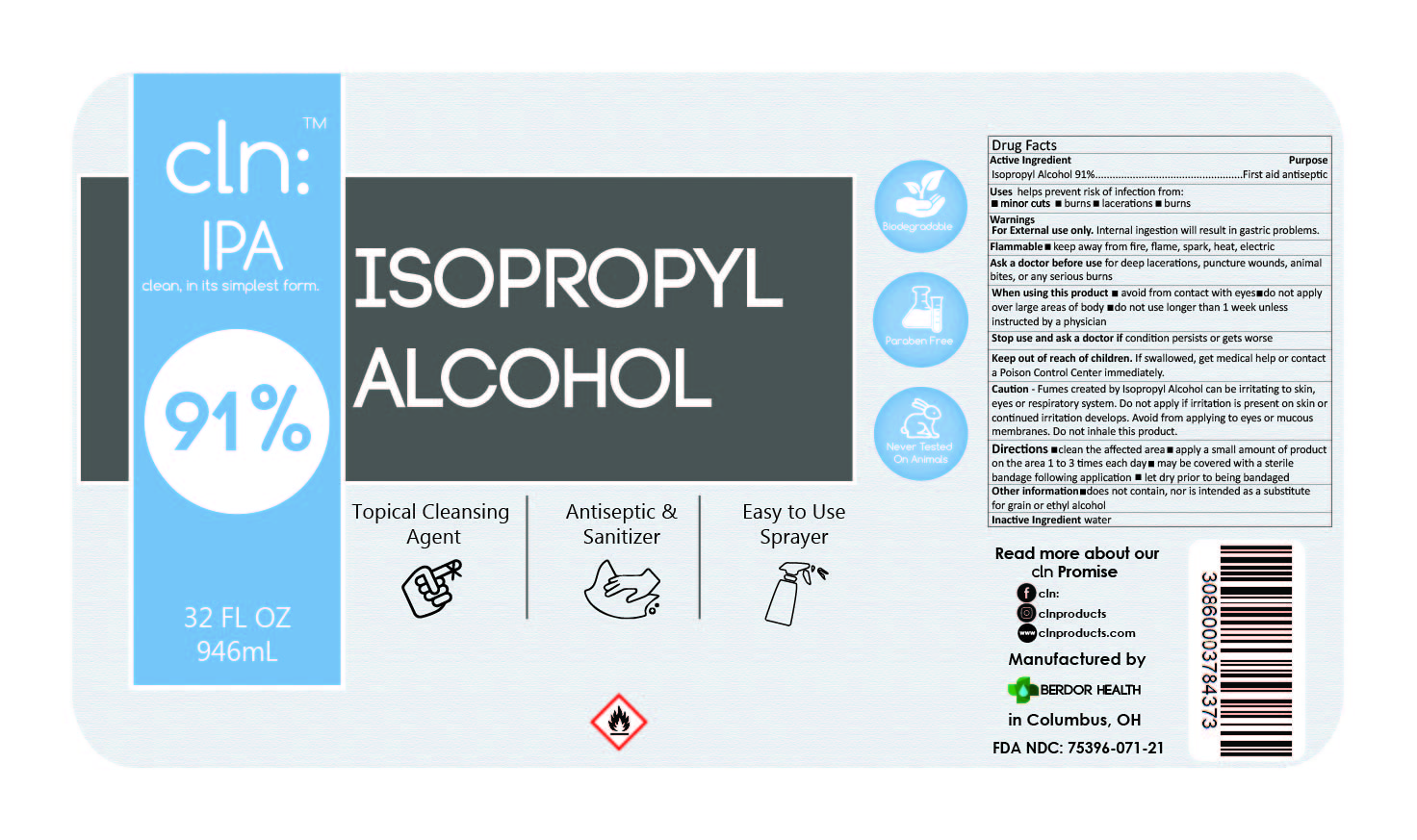 DRUG LABEL: Isopropyl Alcohol
NDC: 75396-071 | Form: LIQUID
Manufacturer: BuckAirways Inc.
Category: otc | Type: HUMAN OTC DRUG LABEL
Date: 20210123

ACTIVE INGREDIENTS: ISOPROPYL ALCOHOL 91 mL/100 mL
INACTIVE INGREDIENTS: WATER

Active Ingredient

Isopropyl Alcohol 91%...................................................First aid antiseptic

Uses

helps prevent risk of infection from:

- minor cuts
- burns
- lacerations
- burns

Warnings

For External use only. Internal ingestion will result in gastric problems.

Flammable

- keep away from fire, flame, spark, heat, electric

Ask a doctor before use

for deep lacerations, puncture wounds, animal bites, or any serious burns

When using this product

- avoid from contact with eyes
- do not apply over large areas of body
- do not use longer than 1 week unless instructed by a physician

Stop use and ask a doctor if

condition persists or gets worse

Keep out of reach of children.

If swallowed, get medical help or contact a Poison Control Center immediately.

Caution

Fumes created by Isopropyl Alcohol can be irritating to skin, eyes, or respiratory system. Do not apply if irritation is present on skin or continued irritation develops. Avoid from applying to eyes or mucous membranes. Do not inhale this product.

Directions

- clean the affected area
- apply a small amount of product on the area 1 to 3 times each day
- may be covered with a sterile
- bandage following application
- let dry prior to being bandaged

Other Information

- does not contain, nor is intended as a substitute for grain or ethyl alcohol

Inactive Ingredient

water

75396-071-18 LABEL PANEL

75396-071-20 LABEL PANEL

75396-071-21 LABEL PANEL